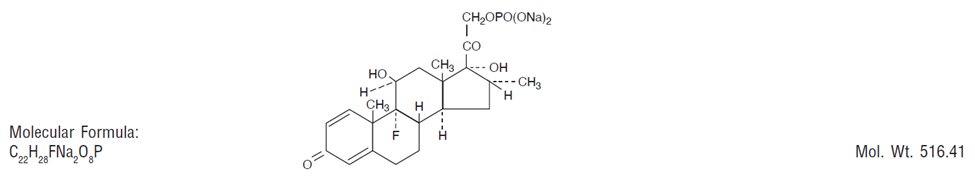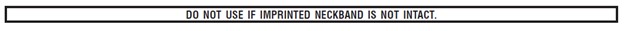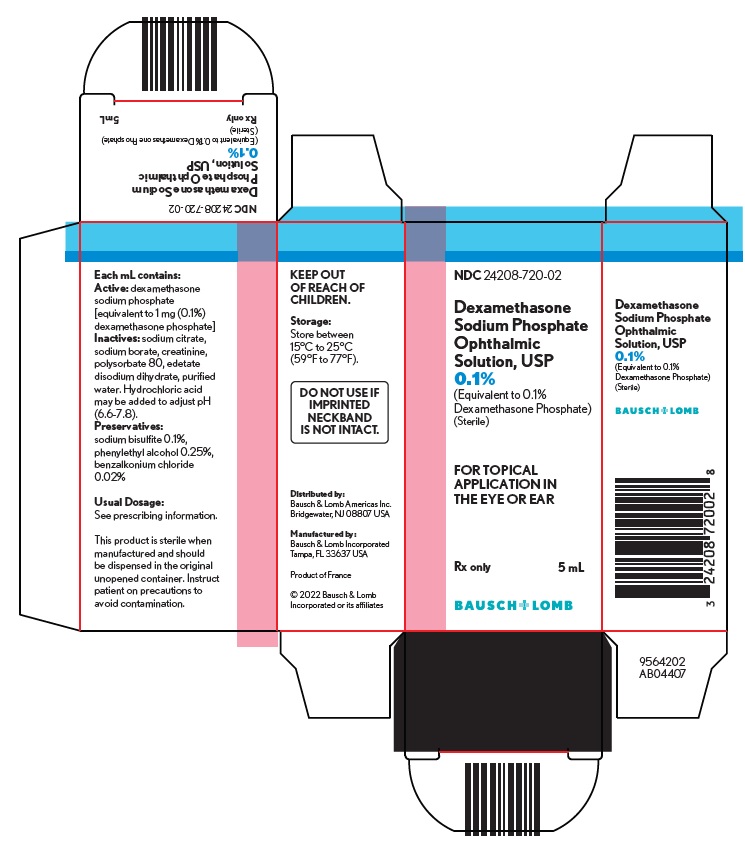 DRUG LABEL: Dexamethasone Sodium Phosphate
NDC: 24208-720 | Form: SOLUTION/ DROPS
Manufacturer: Bausch & Lomb Incorporated
Category: prescription | Type: HUMAN PRESCRIPTION DRUG LABEL
Date: 20220831

ACTIVE INGREDIENTS: DEXAMETHASONE SODIUM PHOSPHATE 1 mg/1 mL
INACTIVE INGREDIENTS: BENZALKONIUM CHLORIDE; CREATININE; EDETATE DISODIUM; HYDROCHLORIC ACID; PHENYLETHYL ALCOHOL; POLYSORBATE 80; WATER; SODIUM BISULFITE; SODIUM BORATE; SODIUM CITRATE, UNSPECIFIED FORM

Dexamethasone Sodium Phosphate
Ophthalmic Solution, USP
0.1%
(Equivalent to 0.1% Dexamethasone Phosphate)
(Sterile)

DESCRIPTION

Dexamethasone sodium phosphate ophthalmic solution is a clear, colorless to pale yellow topical steroid solution for ophthalmic or otic administration.

Glucocorticoids are adrenocortical steroids, both naturally occurring and synthetic. Dexamethasone is a synthetic analog of naturally occurring glucocorticoids (hydrocortisone and cortisone). Dexamethasone sodium phosphate is a water soluble, inorganic ester of dexamethasone. It is approximately three thousand times more soluble in water at 25°C than hydrocortisone.

Chemical Name: 9-fluoro-11β, 17-dihydroxy-16α-methyl-21-[phosphonooxy]pregna-1,4-diene-3, 20-dione disodium salt.

Each mL contains: Active: dexamethasone sodium phosphate [equivalent to 1 mg (0.1%) dexamethasone phosphate]. Inactives: sodium citrate, sodium borate, creatinine, polysorbate 80, edetate disodium dihydrate, purified water. Hydrochloric acid may be added to adjust pH (6.6-7.8).
Preservatives: sodium bisulfite 0.1%, phenylethyl alcohol 0.25%, benzalkonium chloride 0.02%.

CLINICAL PHARMACOLOGY

Dexamethasone sodium phosphate suppresses the inflammatory response to a variety of agents and it probably delays or slows healing. No generally accepted explanation of these steroid properties has been advanced.

INDICATIONS AND USAGE

For the treatment of the following conditions:

Ophthalmic: Steroid responsive inflammatory conditions of the palpebral and bulbar conjunctiva, cornea, and anterior segment of the globe, such as allergic conjunctivitis, acne rosacea, superficial punctate keratitis, herpes zoster keratitis, iritis, cyclitis, selected infective conjunctivitis when the inherent hazard of steroid use is accepted to obtain an advisable diminution in edema and inflammation; corneal injury from chemical or thermal burns, or penetration of foreign bodies.

Otic: Steroid responsive inflammatory conditions of the external auditory meatus, such as allergic otitis externa, selected purulent and nonpurulent infective otitis externa when the hazard of steroid use is accepted to obtain an advisable diminution in edema and inflammation.

CONTRAINDICATIONS

Epithelial herpes simplex keratitis (dendritic keratitis). Acute infectious stages of vaccinia, varicella, and many other viral diseases of the cornea and conjunctiva.

Mycobacterial infection of the eye.

Fungal diseases of ocular or auricular structures.

Hypersensitivity to any component of this product, including sulfites (see WARNINGS).

Perforation of a drum membrane.

WARNINGS

Prolonged use may result in ocular hypertension and/or glaucoma, with damage to the optic nerve, defects in visual acuity and fields of vision, and posterior subcapsular cataract formation. Prolonged use may suppress the host response and thus increase the hazard of secondary ocular infections. In those diseases causing thinning of the cornea or sclera, perforations have been known to occur with the use of topical corticosteroids. In acute purulent conditions of the eye or ear, corticosteroids may mask infection or enhance existing infection. If these products are used for 10 days or longer, intraocular pressure should be routinely monitored even though it may be difficult in children and uncooperative patients.

Employment of corticosteroid medication in the treatment of herpes simplex other than epithelial herpes simplex keratitis, in which it is contraindicated, requires great caution; periodic slit-lamp microscopy is essential.

This product contains sodium bisulfite, a sulfite that may cause allergic-type reactions including anaphylactic symptoms and life-threatening or less severe asthmatic episodes in certain susceptible people. The overall prevalence of sulfite sensitivity in the general population is unknown and probably low. Sulfite sensitivity is seen more frequently in asthmatic than in nonasthmatic people.

PRECAUTIONS

General

The possibility of persistent fungal infections of the cornea should be considered after prolonged corticosteroid dosing.

There have been reports of bacterial keratitis associated with the use of multiple dose containers of topical ophthalmic products. These containers had been inadvertently contaminated by patients who, in most cases, had a concurrent corneal disease or a disruption of the ocular epithelial surface (see PRECAUTIONS, Information for Patients).

Information for Patients

Patients should be instructed to avoid allowing the tip of the dispensing container to contact the eye or surrounding structures.

Patients should also be instructed that ocular solutions, if handled improperly, can become contaminated by common bacteria known to cause ocular infections. Serious damage to the eye and subsequent loss of vision may result from using contaminated solutions (see PRECAUTIONS, General).

Patients should also be advised that if they develop an intercurrent ocular condition (e.g., trauma, ocular surgery or infection), they should immediately seek their physician’s advice concerning the continued use of the present multidose container.

One of the preservatives in dexamethasone sodium phosphate ophthalmic solution, benzalkonium chloride, may be absorbed by soft contact lenses. Patients wearing soft contact lenses should be instructed to wait at least 15 minutes after instilling dexamethasone sodium phosphate ophthalmic solution before they insert their lenses.

Carcinogenesis, Mutagenesis, Impairment of Fertility

Long-term animal studies have not been performed to evaluate the carcinogenic potential or the effect on fertility of dexamethasone sodium phosphate ophthalmic solution.

Pregnancy

Dexamethasone has been shown to be teratogenic in mice and rabbits following topical ophthalmic application in multiples of the therapeutic dose.

In the mouse, corticosteroids produce fetal resorptions and a specific abnormality, cleft palate. In the rabbit, corticosteroids have produced fetal resorptions and multiple abnormalities involving the head, ears, limbs, palate, etc.

There are no adequate or well-controlled studies in pregnant women. Dexamethasone sodium phosphate ophthalmic solution should be used during pregnancy only if the potential benefit to the mother justifies the potential risk to the embryo or fetus. Infants born of mothers who have received substantial doses of corticosteroids during pregnancy should be observed carefully for signs of hypoadrenalism.

Nursing Mothers

Topically applied steroids are absorbed systemically. Therefore, because of the potential for serious adverse reactions in nursing infants from dexamethasone sodium phosphate, a decision should be made whether to discontinue nursing or discontinue the drug, taking into account the importance of the drug to the mother.

Pediatric Use

Safety and effectiveness in pediatric patients have not been established.

Geriatric Use

No overall differences in safety and effectiveness have been observed between elderly and younger patients.

ADVERSE REACTIONS

Glaucoma with optic nerve damage, visual acuity and field defects, posterior subcapsular cataract formation, secondary ocular infection from pathogens including herpes simplex, perforation of the globe.

Rarely, filtering blebs have been reported when topical steroids have been used following cataract surgery.

Rarely, stinging or burning may occur.

To report SUSPECTED ADVERSE REACTIONS, contact Bausch & Lomb Incorporated at 1-800-553-5340 or FDA at 1-800-FDA-1088 or www.fda.gov/medwatch.

DOSAGE AND ADMINISTRATION

The duration of treatment will vary with the type of lesion and may extend from a few days to several weeks, according to therapeutic response. Relapses, more common in chronic active lesions than in self-limited conditions, usually respond to treatment.

Eye: Instill one or two drops of solution into the conjunctival sac every hour during the day and every two hours during the night as initial therapy. When a favorable response is observed, reduce dosage to one drop every four hours. Later, further reduction in dosage to one drop three or four times daily may suffice to control symptoms.

Ear: Clean the aural canal thoroughly and sponge dry. Instill the solution directly into the aural canal. A suggested initial dosage is three or four drops two or three times a day. When a favorable response is obtained, reduce dosage gradually and eventually discontinue.

If preferred, the aural canal may be packed with a gauze wick saturated with solution. Keep the wick moist with the preparation and remove from the ear after 12 to 24 hours. Treatment may be repeated as often as necessary at the discretion of the physician.

HOW SUPPLIED

Dexamethasone sodium phosphate ophthalmic solution USP, 0.1% is supplied in a plastic squeeze bottle with a white cap and a controlled drop tip in the following size: 5 mL fill in a 10 mL bottle - NDC 24208-720-02

Storage: Store between 15°C to 25°C (59°F to 77°F).

Keep out of reach of children.

Distributed by:
Bausch & Lomb Americas Inc.
Bridgewater, NJ 08807 USA

Manufactured by:
Bausch & Lomb Incorporated
Tampa, FL 33637 USA

© 2022 Bausch & Lomb Incorporated or its affiliates

Revised: August 2022

9100205 (Folded)
9100305 (Flat)

PACKAGE/LABEL PRINCIPAL DISPLAY PANEL

NDC 24208-720-02

Dexamethasone
Sodium Phosphate
Ophthalmic
Solution, USP
0.1%
(Equivalent to 0.1%
Dexamethasone Phosphate)
(Sterile)

FOR TOPICAL
APPLICATION IN
THE EYE OR EAR

Rx only

5 mL

BAUSCH + LOMB

9564202
AB04407